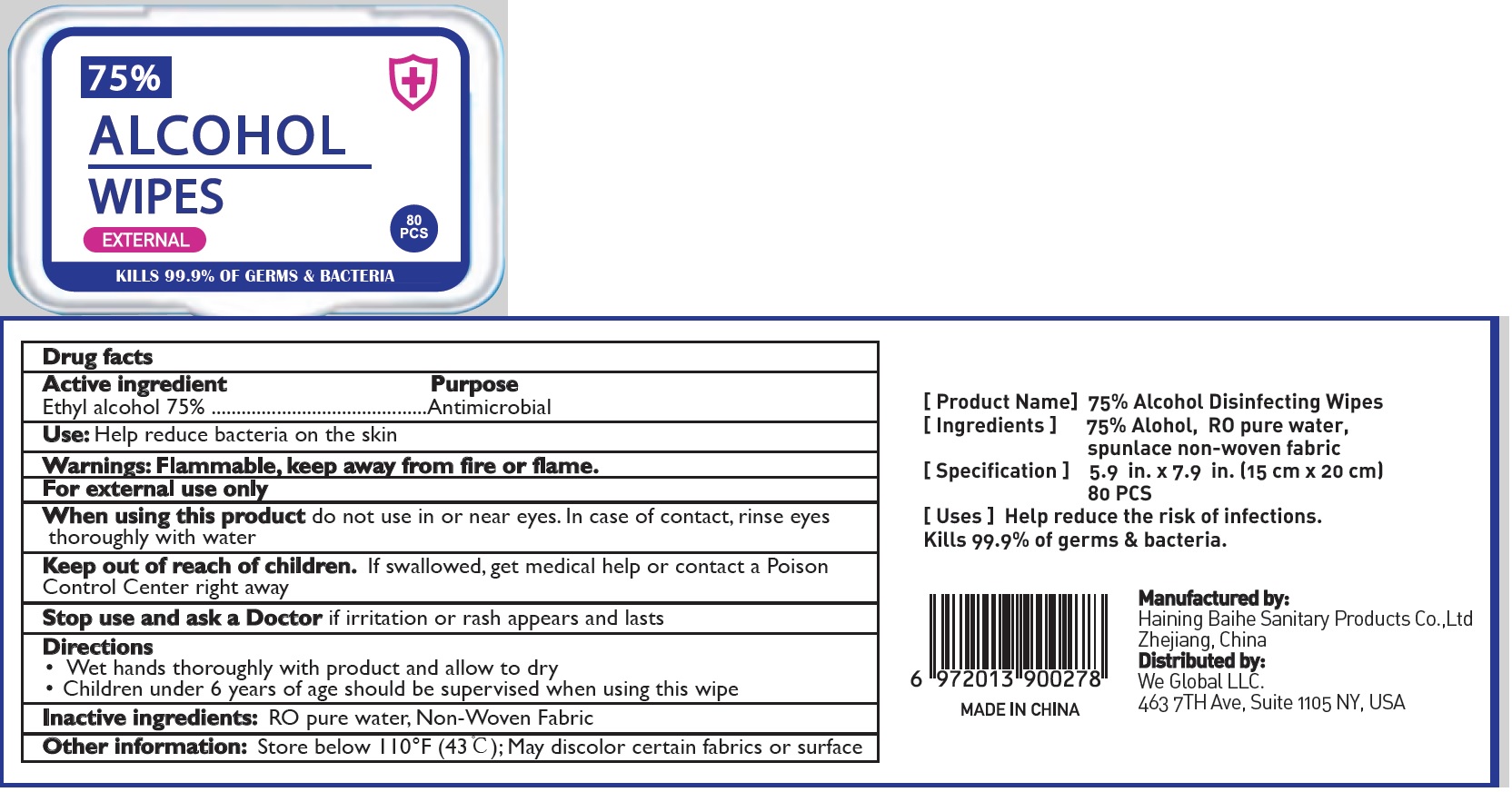 DRUG LABEL: Alcohol Wipes
NDC: 77435-006 | Form: SWAB
Manufacturer: Haining Baihe Sanitary Products Co., Ltd.
Category: otc | Type: HUMAN OTC DRUG LABEL
Date: 20200512

ACTIVE INGREDIENTS: ALCOHOL 75 g/100 g
INACTIVE INGREDIENTS: WATER

alcohol Wipes

Active Ingredient

Ethyl Alcohol 75%

Purpose

Antimicrobial

USE

●Help reduce bacteria on the skin.

Warning

- Flammable, keep away from fire or flame. For external use only.
- When using this product, Do not use in or near the eyes. In case of contact, rinse eyes thoroughly with water.

- Stop use and ask a doctor, if irritaion and rash appears and lasts.

Other Information：

Store below 110℉ (43 ℃); May discolor certain fabrics or surface

KEEP OUT OF REACH OF CHILDREN

●If swallowed, get medical help or contact a Poison Contrl Center right away.

Directions

- Wet hands thoroughluy with produt and allow to dry.
- Children under 6 years of age should be supervised when using this wipe.

Inactive ingredients

RO Pure Water, Non-Woven Fabric.